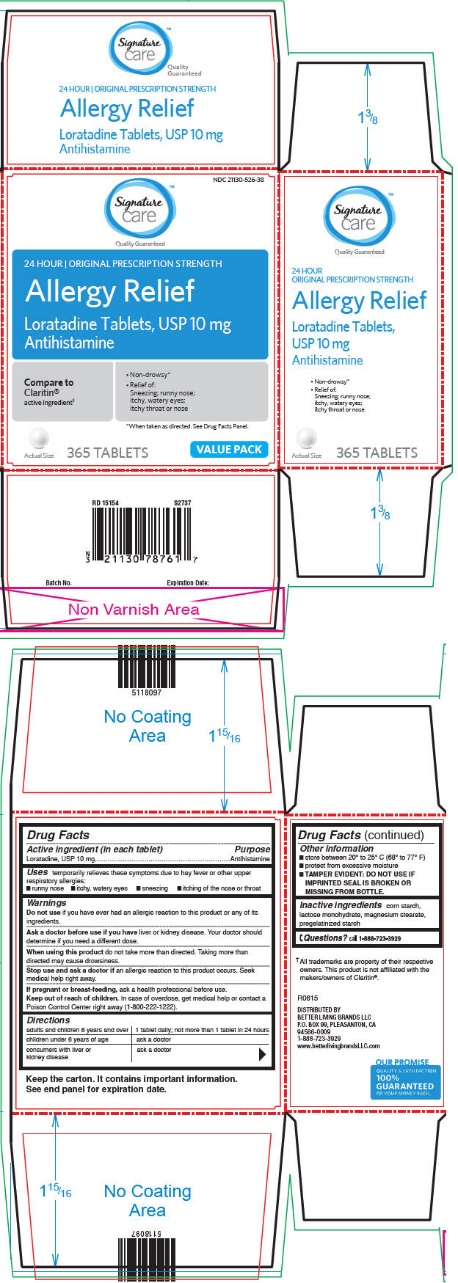 DRUG LABEL: Loratadine
NDC: 21130-526 | Form: TABLET
Manufacturer: SAFEWAY INC.
Category: otc | Type: HUMAN OTC DRUG LABEL
Date: 20211221

ACTIVE INGREDIENTS: LORATADINE 10 mg/1 1
INACTIVE INGREDIENTS: STARCH, CORN; LACTOSE MONOHYDRATE; MAGNESIUM STEARATE

Drug Facts

ACTIVE INGREDIENT (IN EACH TABLET)

Loratadine, USP 10 mg

PURPOSE

Antihistamine

USES

Temporarily relieves these symptoms due to hay fever or other upper respiratory allergies:

- runny nose
- itchy, watery eyes
- sneezing
- itching of the nose or throat

WARNINGS

Do not use

If you have ever had an allergic reaction to this product or any of its ingredients.

Ask a doctor before use if you have

Liver or kidney disease. Your doctor should determine if you need a different dose.

When using this product

Do not take more than directed. Taking more than directed may cause drowsiness.

Stop use and ask a doctor if

An allergic reaction to this product occurs. Seek medical help right away.

If pregnant or breast-feeding,

Ask a health professional before use.

Keep out of reach of children.

In case of overdose, get medical help or contact a Poison Control Center right away (1-800-222-1222).

DIRECTIONS

adults and children 6 years and over | 1 tablet daily; not more than 1 tablet in 24 hours
children under 6 years of age | ask a doctor
consumers with liver or kidney disease | ask a doctor

OTHER INFORMATION

- store between 20° to 25° C (68° to 77° F)
- protect from excessive moisture
- TAMPER EVIDENT: DO NOT USE IF IMPRINTED SEAL IS BROKEN OR MISSING FROM BOTTLE.

INACTIVE INGREDIENTS

Corn starch, lactose monohydrate, magnesium stearate, pregelatinized starch

QUESTIONS OR COMMENTS?

Call 1-888-732-3929

PRINCIPAL DISPLAY PANEL - 10 mg Tablet Bottle Carton

NDC 21130-526-38

Signature
care™
Quality Guaranteed

24 HOUR | ORIGINAL PRESCRIPTION STRENGTH

Allergy Relief

Loratadine Tablets, USP 10 mg
Antihistamine

Compare to
Claritin®
active ingredient†

- Non-drowsy*
- Relief of:
  Sneezing; runny nose;
  itchy, watery eyes;
  itchy throat or nose

*When taken as directed. See Drug Facts Panel.

Actual Size

365 TABLETS

VALUE PACK